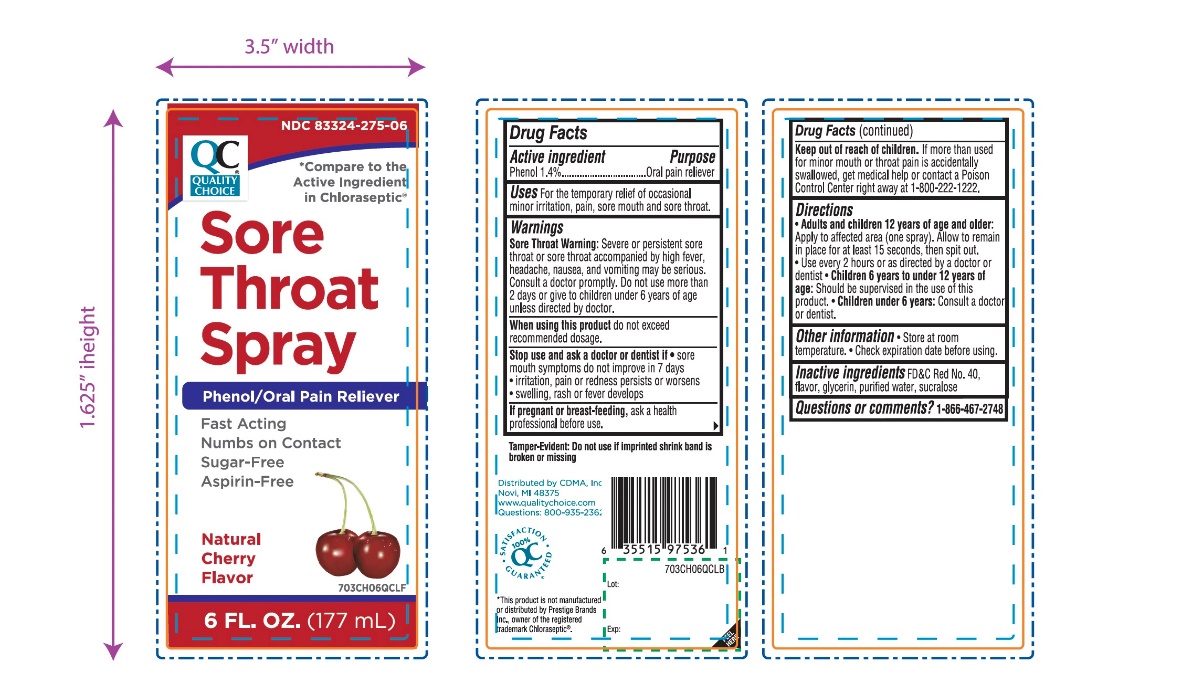 DRUG LABEL: QUALITY CHOICE

NDC: 83324-275 | Form: SPRAY
Manufacturer: CHAIN DRUG MARKETING ASSOCIATION
Category: otc | Type: HUMAN OTC DRUG LABEL
Date: 20250610

ACTIVE INGREDIENTS: PHENOL 1.4 g/100 mL
INACTIVE INGREDIENTS: FD&C RED NO. 40; GLYCERIN; WATER; SUCRALOSE

Quality Choice Sore Throat Spray

Active ingredient

Phenol 1.4%

Purpose

Oral pain reliever

Uses

For the temporarily relief of occasional minor irritation, pain, sore mouth and sore throat.

Warnings

Sore throat warning:Severe or persistent sore throat or sore throat accompanied by high fever, headache, nausea, and vomiting may be serious. Consult a doctor promptly. Do not use more than 2 days or administer to children under 6 years of age unless directed by a doctor.

When using this product,

do not exceed recommended dosage.

Stop use and ask a dentist or doctor if

- sore mouth symptoms do not improve in 7 days
- irritation, pain or redness persists or worsens
- swelling, rash or fever develops

If pregnant or breast-feeding,

ask a doctor before use.

Keep out of reach of children.

If more than used for minor mouth or throat pain is accidentally swallowed ,get medical help or contact a Poison Control Center right away at 1-800-222-1222.

Directions

- Adults and children 12 years of age and older:
  - apply to affected area (one spray)
  - allow to remain in place for at least 15 seconds, then spit out
  - use every 2 hours as directed by a doctor or dentist
- Children 6 years to under 12 years of age: should be supervised in the use of this product
- Children under 6 years of age: Consult a doctor or dentist

Other information

- Store at room temperature.
- Check expiration date before using.

Inactive ingredients

FD&C Red No. 40, flavor, glycerin, purified water, sucralose.

Questions or comments?

1-866-467-2748

Principal Display Panel

QUALITY CHOICE®

*Compare to the active ingredient chloraseptic®

NDC# 83324-275-06

Sore Throat Spray

Phenol/Oral Pain Reliever

Fast Acting

Numbs on Contact

Sugar-Free

Aspirin-Free

Natural Cherry Flavor

6 FL OZ (177 mL)

100% SATISFACTION GUARANTEED

*This product is not manufactured or distributed by Prestige Brands Inc., owner of registered trademark Chloraseptic®.

Tamper - Evident: Do not use if imprinted shrink band is broken or missing

Distributed by CDMA, Inc

Novi, MI 48375

www.qualitychoice.com

Questions: 800-935-236